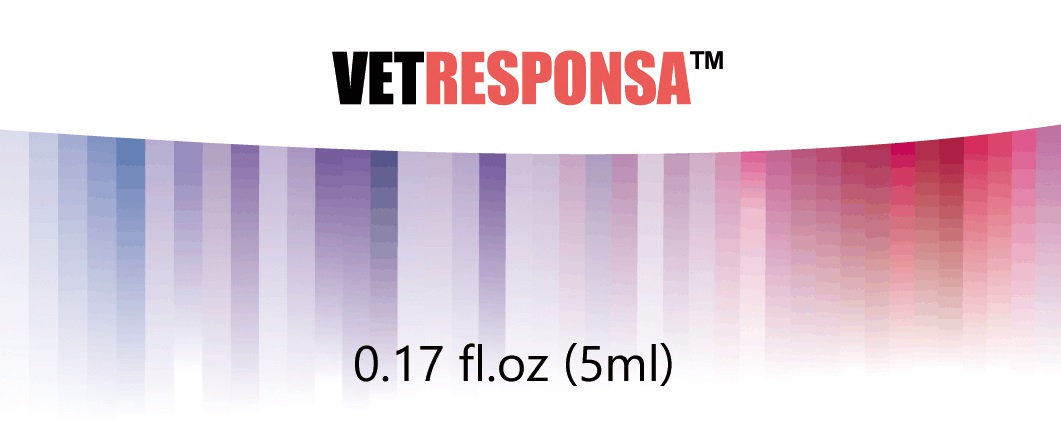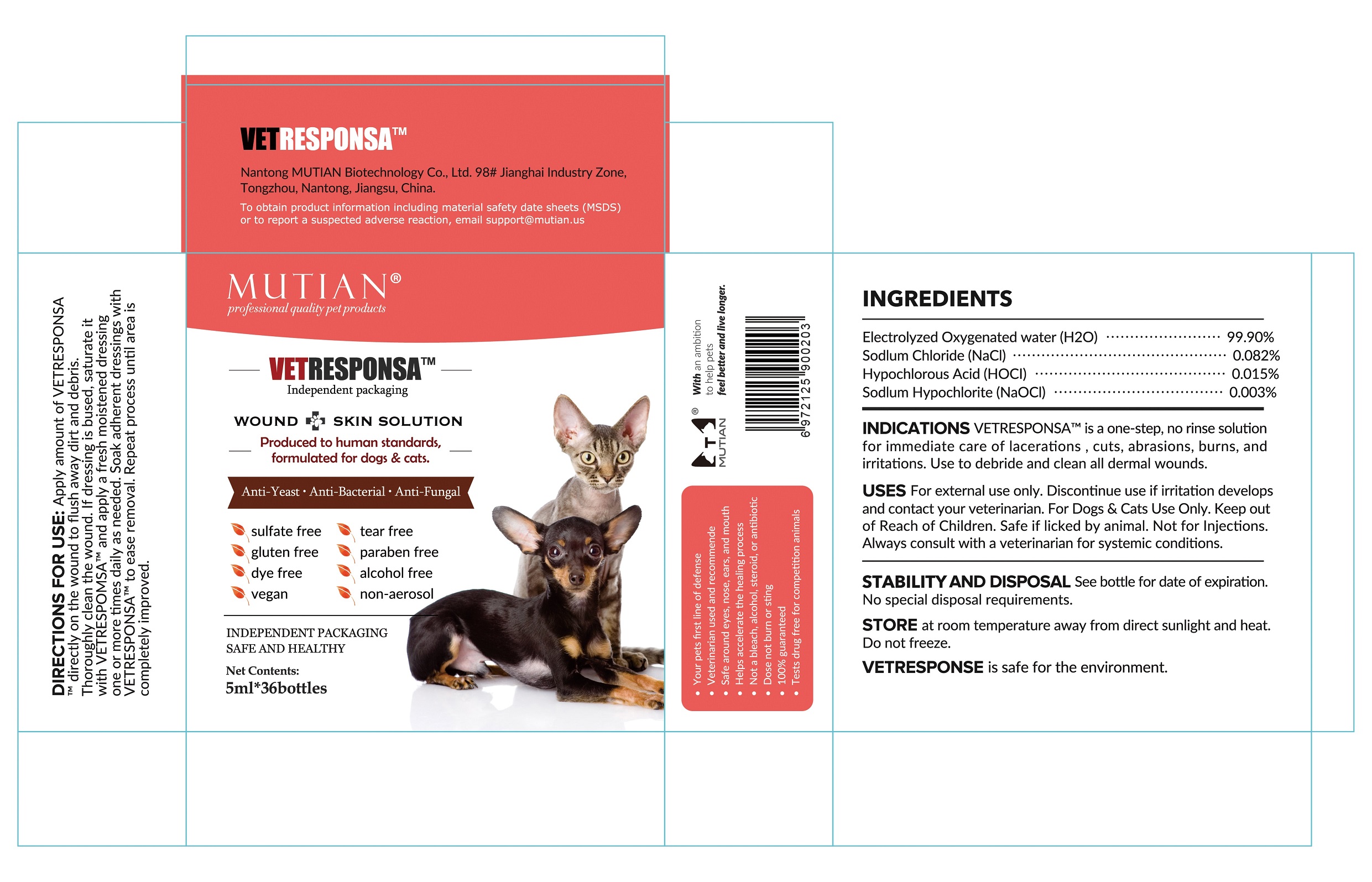 DRUG LABEL: MUTIAN VETRESPONSA
NDC: 73452-215 | Form: LIQUID
Manufacturer: Nantong MUTIAN Biotechnology Co., Ltd
Category: animal | Type: OTC ANIMAL DRUG LABEL
Date: 20200110

ACTIVE INGREDIENTS: Sodium Chloride 0.0041 g/5 mL; Hypochlorous Acid 0.00075 g/5 mL; Sodium Hypochlorite 0.00015 g/5 mL
INACTIVE INGREDIENTS: Water 4.995 mL/5 mL

MuTian, VETRESPONSA, 5mL *36 bottles

WARNINGS AND PRECAUTIONS

For external use only.
For Dogs & Cats Use Only.
Keep out of Reach of Children.
Not for Injections.
Discontinue use if irritation develops and contact your veterinarian.
Always consult with a veterinarian for systemic conditions.

INDICATIONS AND USAGE

VETRESPONSATM is a one-stop, no rinse solution for immediate care of lacerations, cuts, abrasions, burns, and irritations. Use to debride and clean all dermal wounds.
Apply amount of VETRESPONSATM directly on the wound to flush away dirt and debris.
Thoroughly clean the wound. If dressing is bused, saturate it with VETRESPONSATM and apply a fresh moistened dressing one or more times daily as needed. Soak adherent dressings with VETRESPONSATM to ease removal. Repeat process until area is completely improved.

DOSAGE AND ADMINISTRATION

Proper amount per time.
One or more times daily as needed.

ACTIVE INGREDIENT

Sodium Chloride
Hypochlorous Acid
Sodium Hypochlorite

INACTIVE INGREDIENT

Electrolyzed Oxygenated Water

Keep out of reach of children.

STORAGE AND HANDLING

Store at the room temperature away from direct sunlight and heat. Do not freeze.
See bottle for date of expiation. No special disposal requirements.

Package Label

Container Label